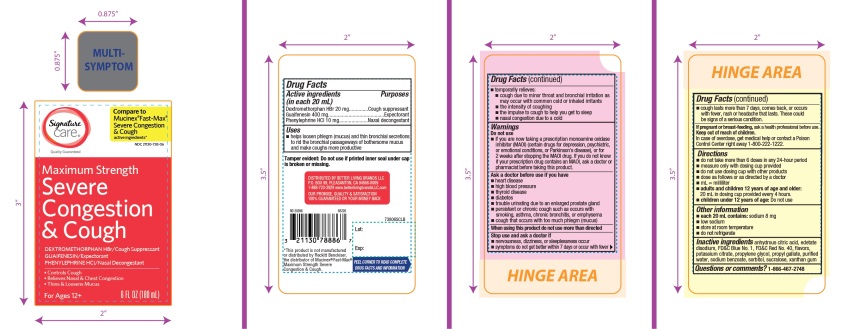 DRUG LABEL: Maximum Strength Severe Congestion and Cough
NDC: 21130-738 | Form: LIQUID
Manufacturer: SAFEWAY
Category: otc | Type: HUMAN OTC DRUG LABEL
Date: 20251029

ACTIVE INGREDIENTS: DEXTROMETHORPHAN HYDROBROMIDE 20 mg/20 mL; GUAIFENESIN 400 mg/20 mL; PHENYLEPHRINE HYDROCHLORIDE 10 mg/20 mL
INACTIVE INGREDIENTS: ANHYDROUS CITRIC ACID; EDETATE DISODIUM; FD&C BLUE NO. 1; FD&C RED NO. 40; POTASSIUM CITRATE; PROPYLENE GLYCOL; PROPYL GALLATE; WATER; SODIUM BENZOATE; SORBITOL; SUCRALOSE; XANTHAN GUM

Kroger Maximum Strength Severe Congestion and Cough

Drug Facts

ACTIVE INGREDIENT

PURPOSE

Active ingredients (in each 20 mL) | Purposes
Dextromethorphan HBr 20 mg | Cough suppressant
Guaifenesin 400 mg | Expectorant
Phenylephrine HCl 10 mg | Nasal decongestant

Uses

- helps loosen phlegm (mucus) and thin bronchial secretions to rid the bronchial passageways of bothersome mucus and make coughs more productive
- temporarily relieves:
  - cough due to minor throat and bronchial irritation as may occur with the common cold or inhaled irritants
  - the intensity of coughing
  - the impulse to cough to help you get to sleep
  - nasal congestion due to a cold

Warnings

Do not use

- if you are now taking a prescription monoamine oxidase inhibitor (MAOI) (certain drugs for depression, psychiatric, or emotional conditions, or Parkinson's disease), or for 2 weeks after stopping the MAOI drug. If you do not know if your prescription drug contains an MAOI, ask a doctor or pharmacist before taking this product.

Ask a doctor before use if you have

- heart disease
- high blood pressure
- thyroid disease
- diabetes
- trouble urinating due to an enlarged prostate gland
- persistent or chronic cough such as occurs with smoking, asthma, chronic bronchitis or emphysema
- cough that occurs with too much phlegm (mucus)

When using this product

- do not use more than directed

Stop use and ask a doctor if

- nervousness, dizziness or sleeplessness occur
- symptoms do not get better within 7 days or occur with fever
- cough comes back, or occurs with rash or persistent headache. These could be signs of a serious condition.

PREGNANCY OR BREAST FEEDING

If pregnant or breast-feeding,ask a health professional before use.

Keep out of reach of children.In case of overdose, get medical help or contact a Poison Control Center right away. (1-800-222-1222)

Directions

- do not take more than 6 doses in any 24-hour period
- measure only with dosing cup provided
- do not use dosing cup with other products
- dose as follows or as directed by a doctor
- mL = milliliter
- adults and children 12 years of age and older:20 mL in dosing cup provided every 4 hours.
- children under 12 years of age:Do not use.

Other information

- each 20 mL contains:sodium 8 mg
- low sodium
- store at room temperature
- do not refrigerate

Inactive ingredients

anhydrous citric acid, edetate disodium, FD&C Blue No. 1, FD&C Red No. 40, flavors, potassium citrate, propylene glycol, propyl gallate, purified water, sodium benzoate, sorbitol, sucralose, xanthan gum

Questions or comments?

1-866-467-2748

PRINCIPAL DISPLAY PANEL

NDC 21130-738-06

Compare to Mucinex® Fast- Max® Maximum Strength Severe Congestion & Cough Active Ingredients*

Maximum Strength

Severe Congestion & Cough
Dextromethorphan HBr - Cough Suppressant
Guaifenesin - Expectorant
Phenylephrine HCl - Nasal Decongestant

- Control Cough
- Relieves Nasal and Chest Congestion
- Thins & loosens mucus

For Ages 12+

6 FL OZ (180 mL)

Tamper evident: do not use if printed seal under cap is broken or missing.

*This product is not manufactured or distributed by RB Health (US) LLC, the distributor of Mucinex®and Fast-Max®Maximum Strength Severe Congestion & Cough.

DISTRIBUTED BY BETTER LIVING BRANDS LLC

P.O. BOX 99, PLEASANTON, CA 94566-0009

1-888-723-3929 www.betterlivingbrandsLLC.com

OUR PROMISE, QUALITY & SATISFACTION

100% GUARANTEED OR YOUR MONEY BACK